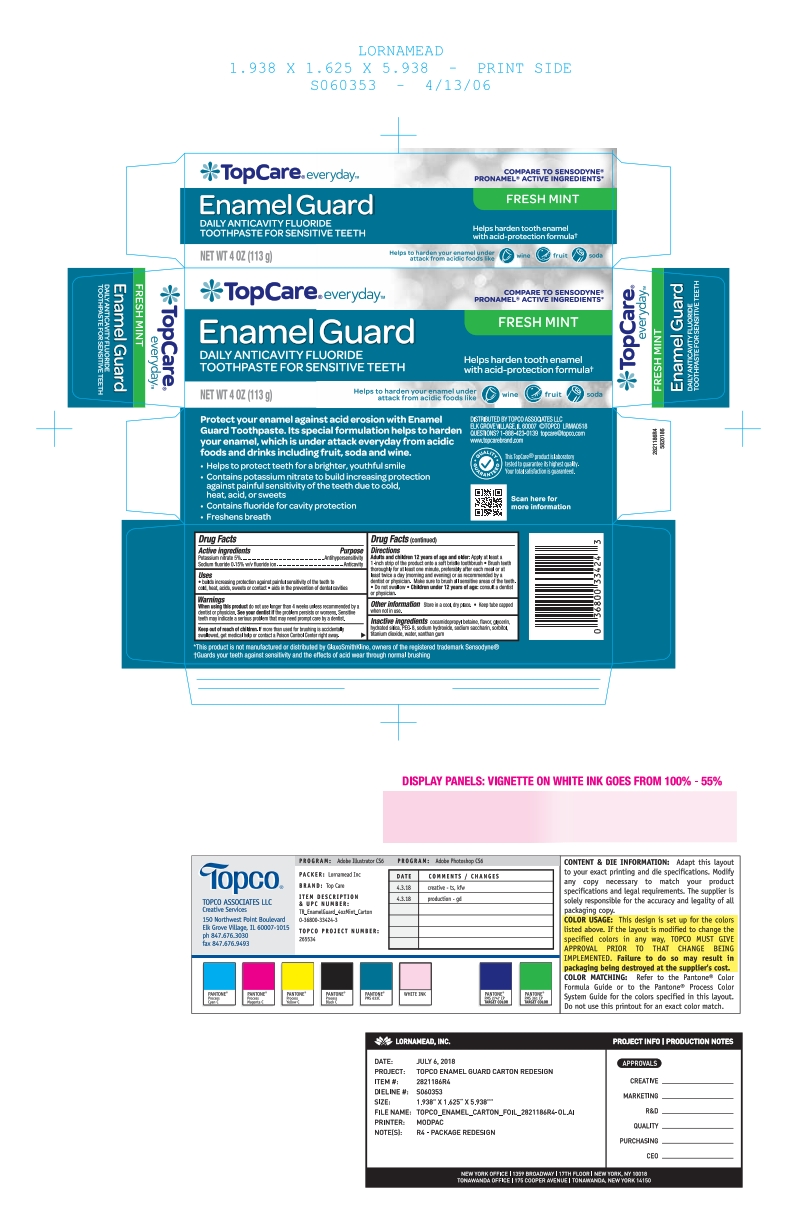 DRUG LABEL: Top Care
NDC: 36800-681 | Form: PASTE, DENTIFRICE
Manufacturer: TOPCO Assoc. LLC
Category: otc | Type: HUMAN OTC DRUG LABEL
Date: 20251114

ACTIVE INGREDIENTS: SODIUM FLUORIDE 0.15 g/100 g; POTASSIUM NITRATE 5 g/100 g
INACTIVE INGREDIENTS: WATER; SACCHARIN SODIUM; SORBITOL; POLYETHYLENE GLYCOL 400; TITANIUM DIOXIDE; SODIUM HYDROXIDE; GLYCERIN; XANTHAN GUM; HYDRATED SILICA; COCAMIDOPROPYL BETAINE; SODIUM METHYL COCOYL TAURATE

5820186 Topco Enamel Guard

Active ingredients / Purpose

Potassium nitrate 5%....................................................Antihypersensitivity

Sodium fluoride 0.15% w/v fluoride ion.........................Anticavity

Uses

- aids in reducing sensitivity
- aids in the prevention of dental cavities

When using this product do not use longer than 4 weeks unless recommended by a dentist or physician. See your dentist if the problem worsens. Sensitive teeth may indicate a serious problem that may need prompt care by a dentist.

Keep out of reach of children. If more than used for brushing is accidentally swallowed, get medical help or contact a Poison Control Center right away.

Directions

Brush teeth thoroughly for at least one minute, preferably after each meal or at least twice a day (morning and evening) or as recommended by a dentist or physican. Make sure to brush all sensitive areas of the teeth. Do not swallow.

DOSAGE AND ADMINISTRATION

Apply at least a 1-inch strip of the product onto a soft bristle toothbrush. Children under 12 years of age: consult a dentist or a doctor.

Other Information

Store in a cool dry place. Keep tube capped when not in use.

Inactive ingredients

cocamidopropyl betaine, flavor, glycerin, hydrated silica, PEG-8, sodium hydroxide, sodium saccharin, sorbitol, titanium dioxide, water, xanthan gum